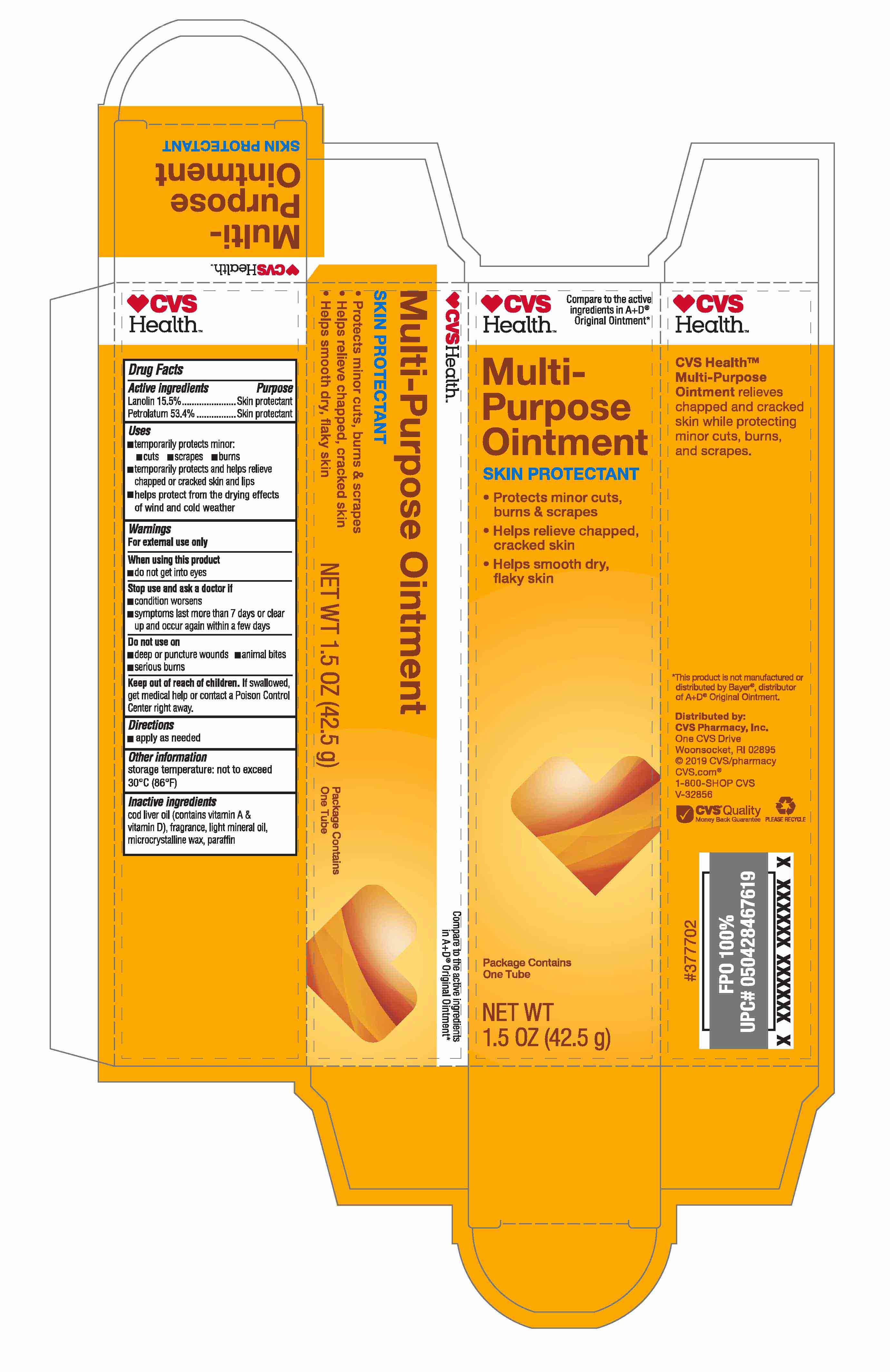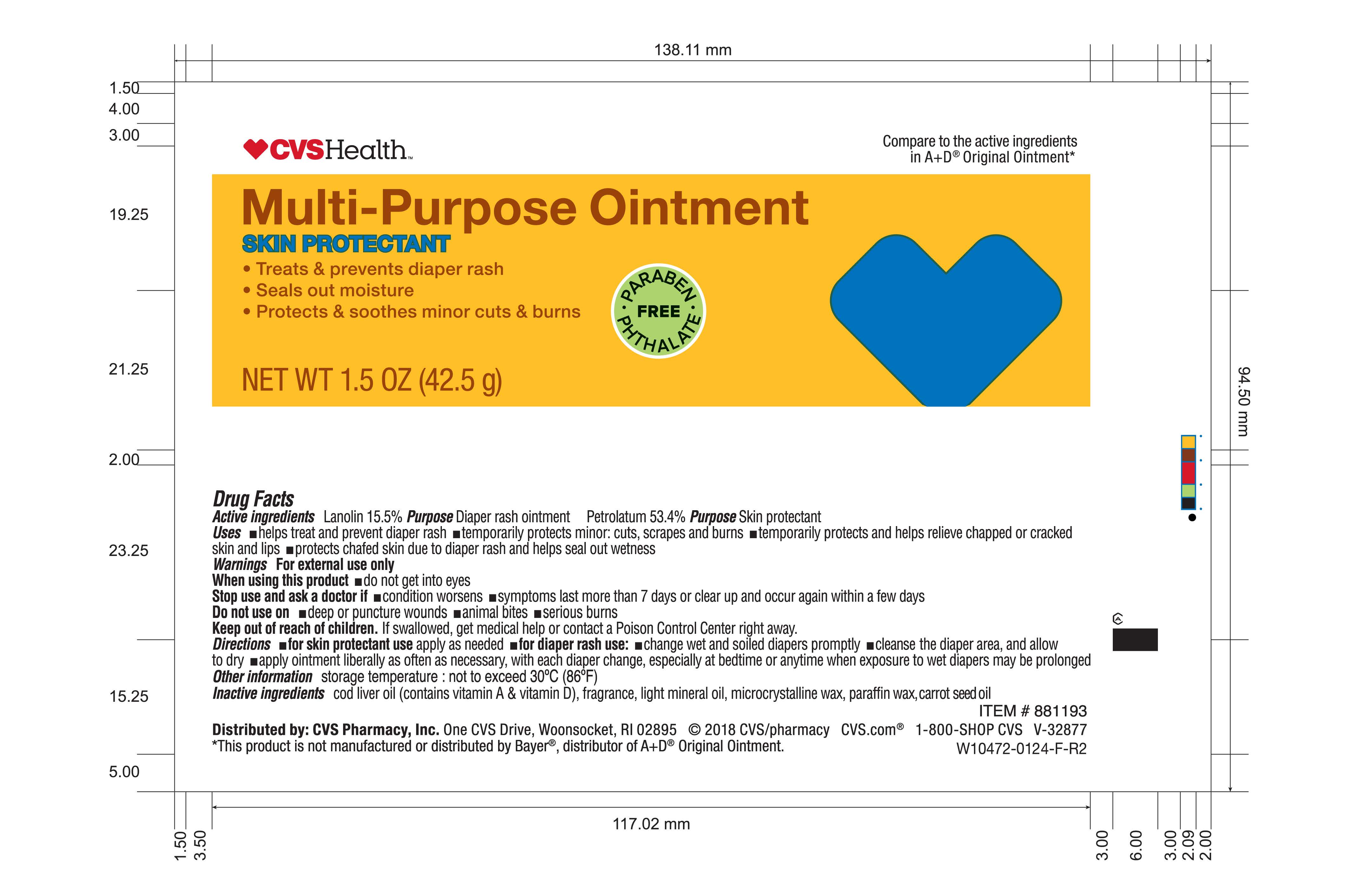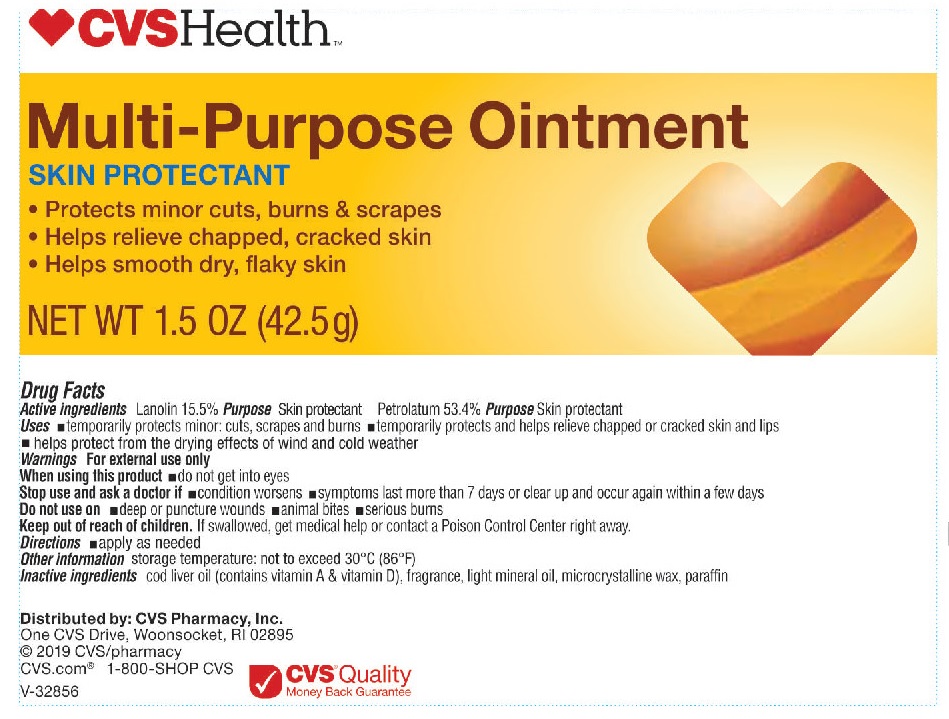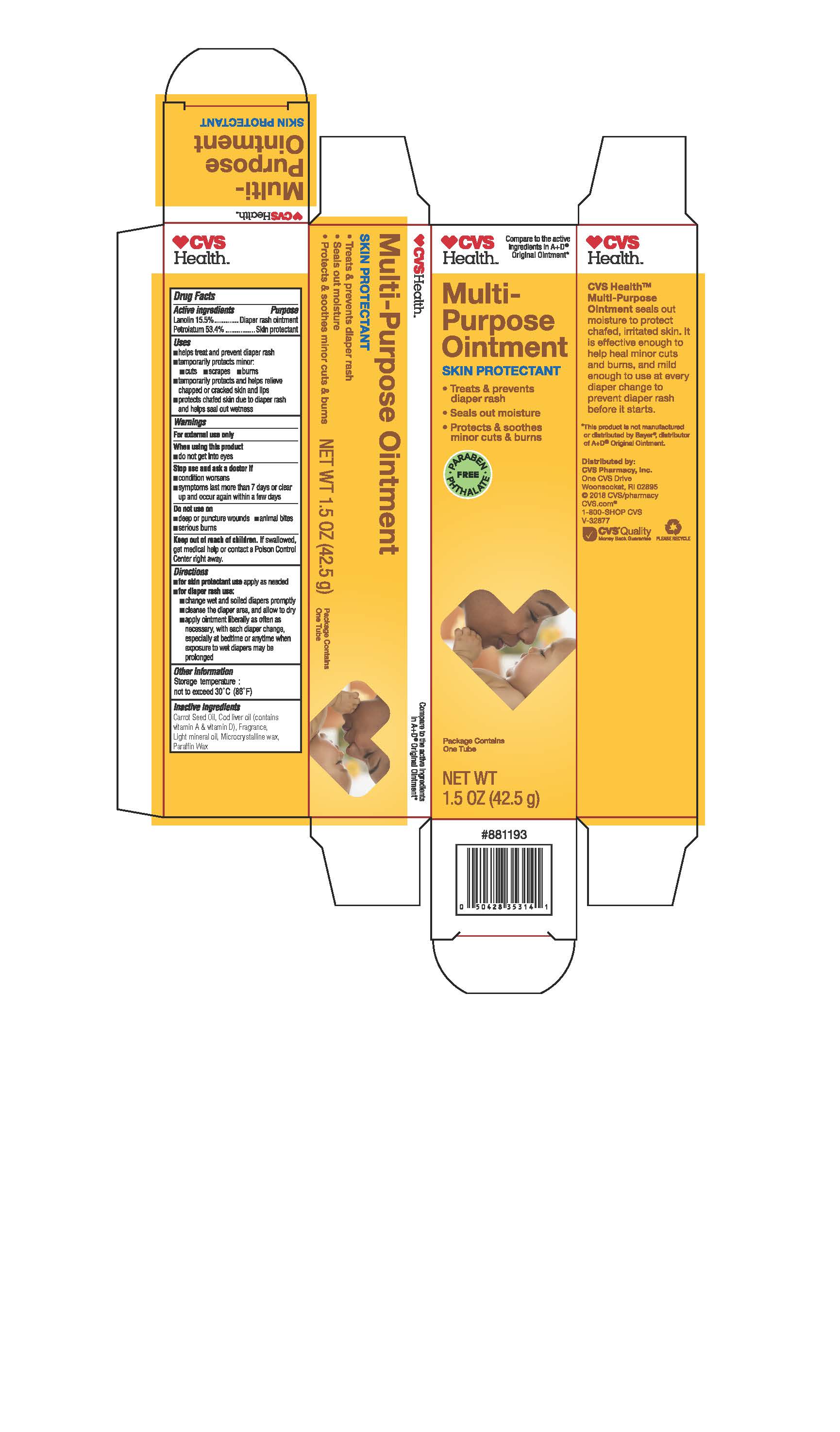 DRUG LABEL: Multi-Purpose Skin Protectant
NDC: 59779-841 | Form: OINTMENT
Manufacturer: CVS Pharmacy
Category: otc | Type: HUMAN OTC DRUG LABEL
Date: 20260114

ACTIVE INGREDIENTS: PETROLATUM 53.4 g/100 g; LANOLIN 15.5 g/100 g
INACTIVE INGREDIENTS: MICROCRYSTALLINE WAX; PARAFFIN; COD LIVER OIL; MINERAL OIL; CARROT SEED OIL

CVS A&D Ointment 1.5oz

Active Ingredients

Lanolin 15.5%

Petrolatum 53.4%

Uses

helps treat and prevent diaper rash, temporarily protects minor: cuts, scrapes and burns, temporarily protects and helps relieve chapped, chafed or cracked skin and lips, protects chafed skin due to diaper rash and helps seal out wetness

Warnings

For external use only.

When using this product

do not get into eyes.

Stop use and ask a doctor if

condition worsens, symptoms last more than 7 days or clear up and occur again within a few days.

Do not use on

deep or puncture wounds, animal bites, serious burns

Keep out of reach of children.

If swallowed, get medical help or contact a Poison Control Center right away.

Directions

for skin protectant use: apply as needed

for diaper rash use: change wet and soiled diapers promptly, cleanse the diaper area and allow to dry, apply ointment liberally as often as necessary, with each diaper change, especially at bedtime or anytime when exposure to wet diapers may be prolonged

Other information

storage temperature: not to exceed 30oC (86oF)

Inactive ingredients

cod liver oil (contains vitamin A & vitamin D), fragrance, light mineral oil, microcrystalline wax, paraffin

Questions?

1-800-SHOP CVS